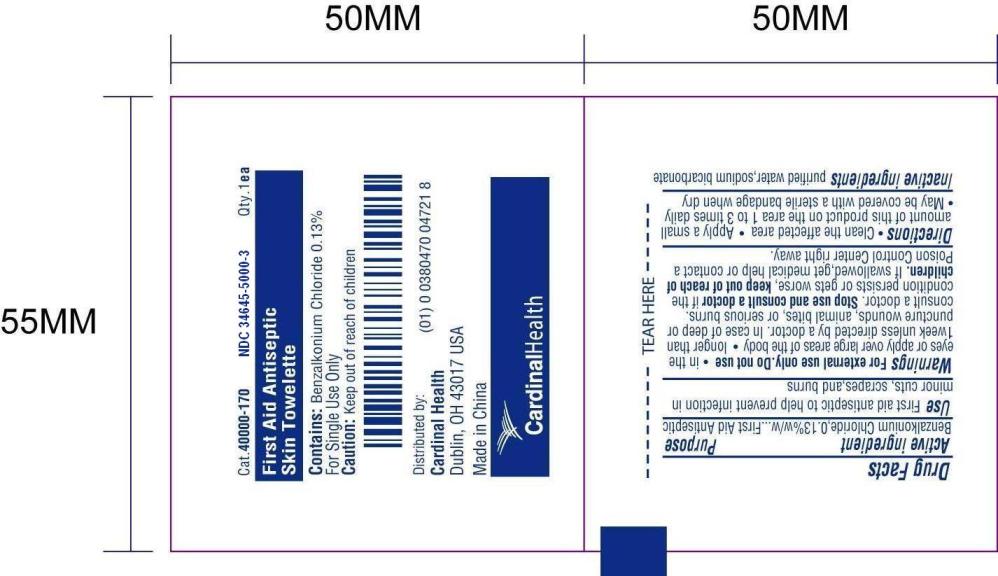 DRUG LABEL: First Aid Antiseptic
NDC: 34645-5000 | Form: SWAB
Manufacturer: Jiangsu Province JianErKang Medical Dressing Co.,Ltd
Category: otc | Type: HUMAN OTC DRUG LABEL
Date: 20100101

ACTIVE INGREDIENTS: BENZALKONIUM CHLORIDE 0.0013 mL/1 mL
INACTIVE INGREDIENTS: WATER 0.9967 mL/1 mL; SODIUM BICARBONATE 0.002 mL/1 mL

Drug Facts

PACKAGE LABEL

Cat. 40000-170 NDC 34645-5000-3 Qty.1ea
First Aid Antiseptic Skin Towelette
Contains: Benzalkonium Chloride 0.13%
For Single Use Only
Caution: Keep out of reach of children
Distributed by:
Cardinal Health
Dublin OH, 43017 USA
Made in China

Active ingredient
Benzalkonium Chloride, 0.13% w/w

Purpose
First Aid Antiseptic

Use
First aid antiseptic to help prevent skin infection in minor cuts, scrapes, and burns

Warnings
For external use only.

Do not use
in the eyes or apply over large areas of the body
longer than 1 week unless directed by a doctor. In case of deep or puncture wounds, animal bites, or serious burns, consult a doctor.

Stop use and consult a doctor
if the condition persists or gets worse

Keep out of reach of children
If swallowed, get medical help or contact a Poison Control Center right away.

Directions
Clean the affected area
Apply a small amount of this product on the area 1 to 3 times daily
May be covered with a sterile bandage when dry

Inactive ingredients
purified water, sodium bicarbonate

Image of Pouch Label